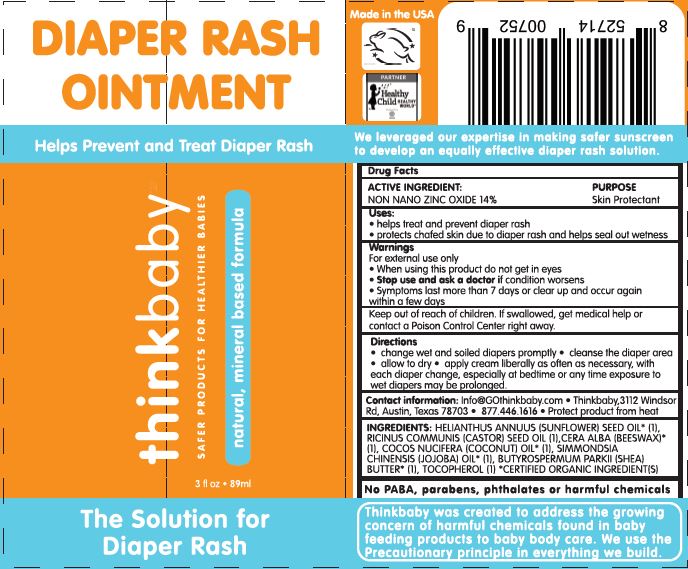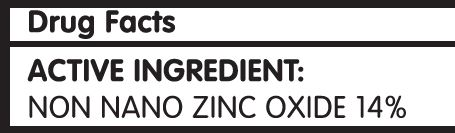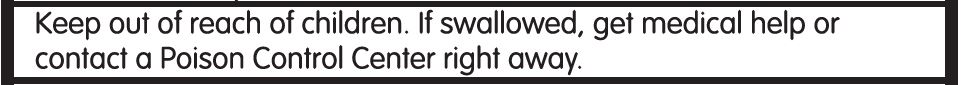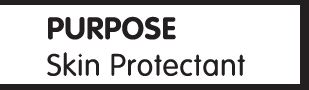 DRUG LABEL: Diaper Cream
NDC: 62932-248 | Form: LOTION
Manufacturer: Private Label Select Ltd CO
Category: otc | Type: HUMAN OTC DRUG LABEL
Date: 20220104

ACTIVE INGREDIENTS: ZINC OXIDE 14 g/100 g
INACTIVE INGREDIENTS: CASTOR OIL; SHEA BUTTER; .BETA.-TOCOPHEROL; SUNFLOWER OIL; COCONUT OIL; .ALPHA.-TOCOPHEROL, D-; .DELTA.-TOCOPHEROL; JOJOBA OIL; WHITE WAX; .GAMMA.-TOCOPHEROL

Think Operations, Think Baby Diaper Rash Ointment